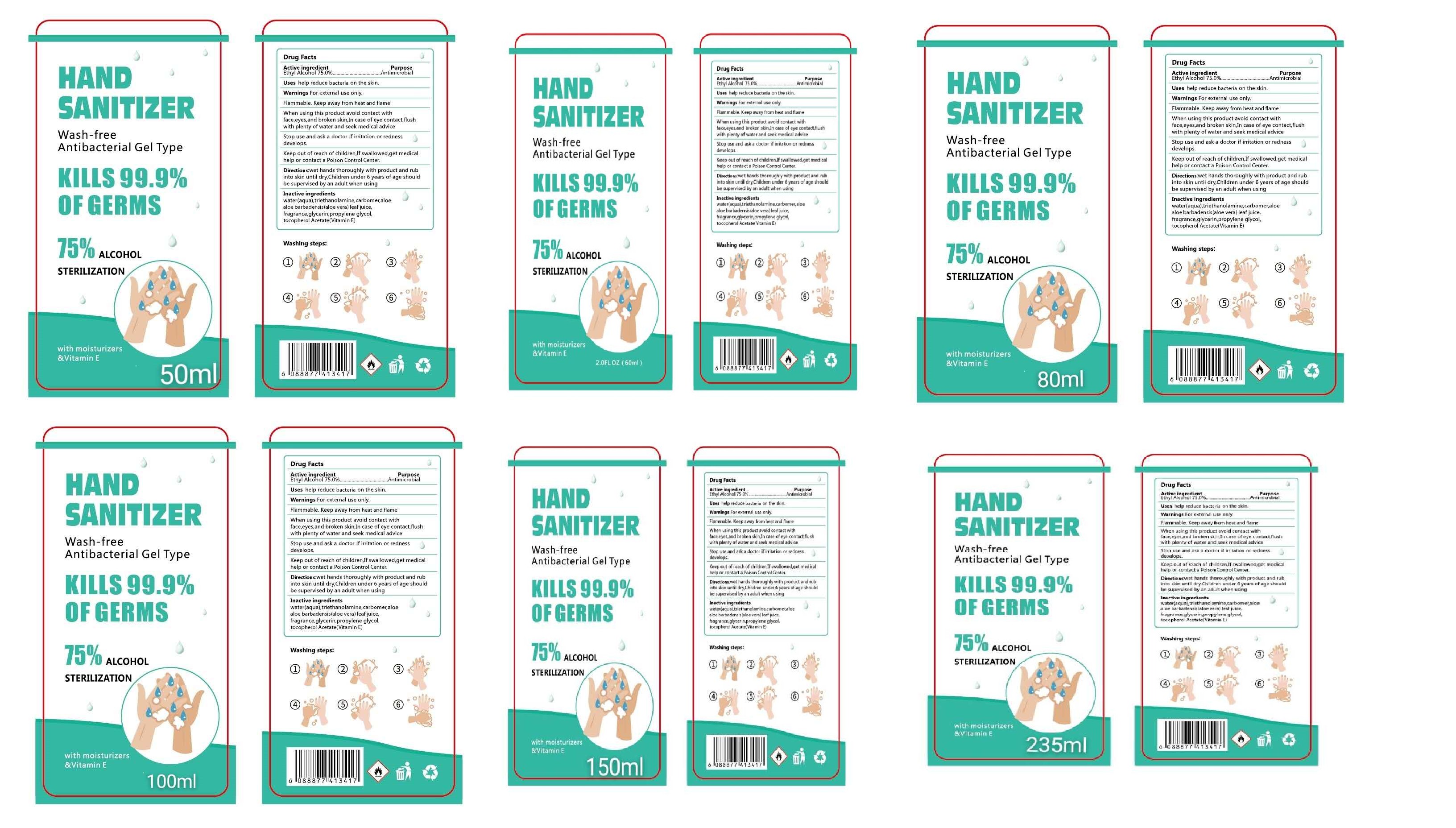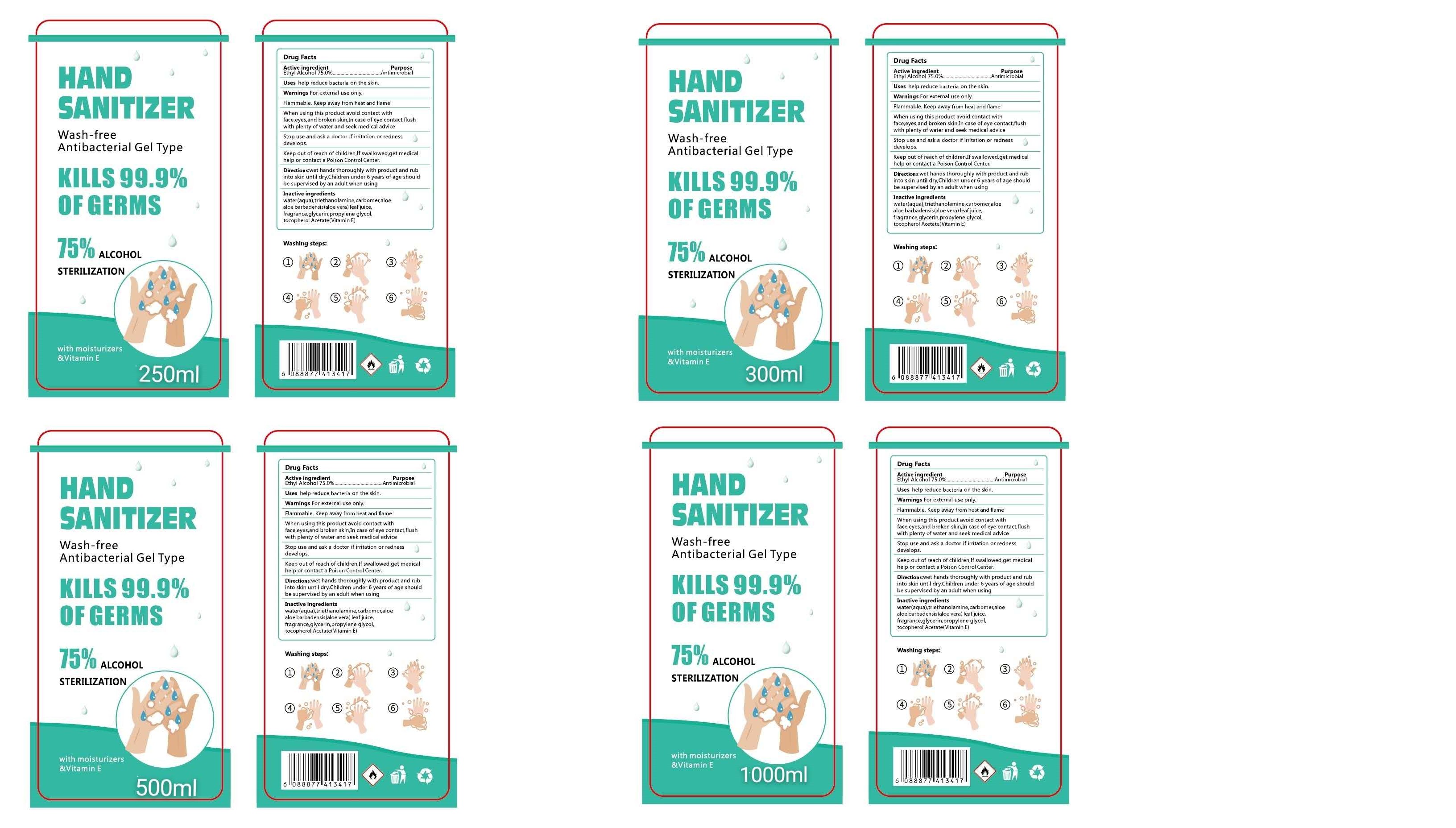 DRUG LABEL: HAND SANITIZER
NDC: 77060-101 | Form: GEL
Manufacturer: Zhejiang Beta Industry And Trade Co., Ltd.
Category: otc | Type: HUMAN OTC DRUG LABEL
Date: 20220412

ACTIVE INGREDIENTS: ALCOHOL 75 mL/100 mL
INACTIVE INGREDIENTS: ALOE VERA LEAF; WATER; PROPYLENE GLYCOL; .ALPHA.-TOCOPHEROL ACETATE, D-; TROLAMINE; GLYCERIN; CARBOMER HOMOPOLYMER TYPE C

Active Ingredient(s)

Ethyl Alcohol 75.0%Antimicrobia

Purpose

Antimicrobial

Use

Uses help reduce bacteria on the skin.

Do not use

- in children less than 2 months of age
- on open skin wounds

When using this product avoid contact with face, eyes, and broken skin, In case of eye contact, flush with plenty of water and seek medical advice

Stop use and ask a doctor if irritation or rash occurs. These may be signs of a serious condition.

Keep out of reach of children, If swallowed, get medical help or contact a Poison Control Center.

Directions

Directions: wet hands thoroughly with product and rubinto skin until dry. Children under 6 years of age should be supervised by an adult when using

Other information

- Store between 15-30C (59-86F)
- Avoid freezing and excessive heat above 40C (104F)

Inactive ingredients

water(aqua), triethanolamine, carbomer, aloealoe barbadensis(aloe vera)leaf juice,fragrance, glycerin, propylene glycol,tocopherol Acetate(Vitamin E)